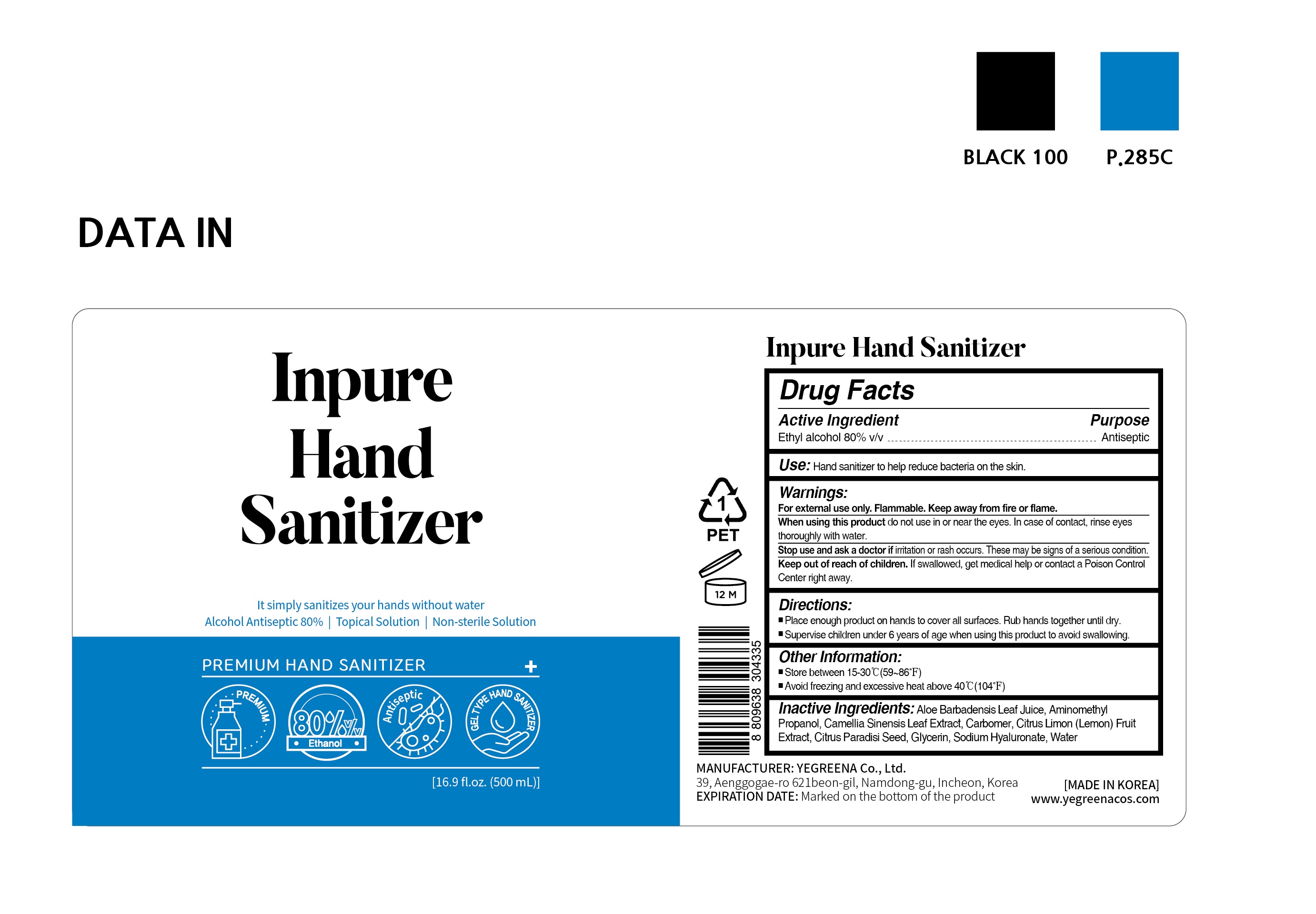 DRUG LABEL: Inpure hand sanitizer
NDC: 78417-101 | Form: GEL
Manufacturer: YEGREENA CO., LTD.
Category: otc | Type: HUMAN OTC DRUG LABEL
Date: 20200604

ACTIVE INGREDIENTS: ALCOHOL 80 mL/100 mL
INACTIVE INGREDIENTS: GLYCERIN; CARBOMER HOMOPOLYMER TYPE B (ALLYL PENTAERYTHRITOL CROSSLINKED); WATER; LEMON OIL; AMINOMETHYLPROPANOL; HYALURONATE SODIUM; ALOE VERA LEAF; CITRUS PARADISI SEED; GREEN TEA LEAF

This is a hand sanitizer manufactured according to the Temporary Policy for Preparation of Certain Alcohol-Based Hand Sanitizer Products During the Public Health Emergency (CoViD-19); Guidance for Industry.

The hand sanitizer is manufactured using only the following United States Pharmacopoeia (USP) grade ingredients in the preparation of the product (percentage in final product formulation) consistent with World Health Organization (WHO) recommendations:

1. Alcohol (ethanol) (USP or Food Chemical Codex (FCC) grade) (80%, volume/volume (v/v)) in an aqueous solution denatured according to Alcohol and Tobacco Tax and Trade Bureau regulations in 27 CFR part 20.
2. Glycerol (1.45% v/v).
3. Hydrogen peroxide (0.125% v/v).
4. Sterile distilled water or boiled cold water.

The firm does not add other active or inactive ingredients. Different or additional ingredients may impact the quality and potency of the product.

Active Ingredient(s)

Alcohol 80% v/v. Purpose: Antiseptic

Purpose

Antiseptic

Use

Hand Sanitizer to help reduce bacteria on the skin.

Warnings

For external use only. Flammable. Keep away from fire or flame.

When using this product do not use in or near the eyes. In case of contact with eyes, rinse eyes thoroughly with water.

Stop use and ask a doctor if irritation or rash appears and lasts.

Keep out of reach of children. If swallowed, get medical help or contact a Poison Control Center right away.

Directions

- Place enough product on your palm to thoroughly cover your hands.
- Rub hands together briskly until dry.
- Children under 6 years of age should be supervised when using this product.

Inactive ingredients

Water, Citrus Limon (Lemon) Fruit Extract, Carbomer, Glycerin, Aminomethyl Propanol, Aloe Barbadensis Leaf Juice, Citrus Paradisi Seed, Camellia Sinensis Leaf Extract, Sodium Hyaluronate

Other information

- Store between 15-30C (59-86F)
- May discolor certain fabrics or surfaces.